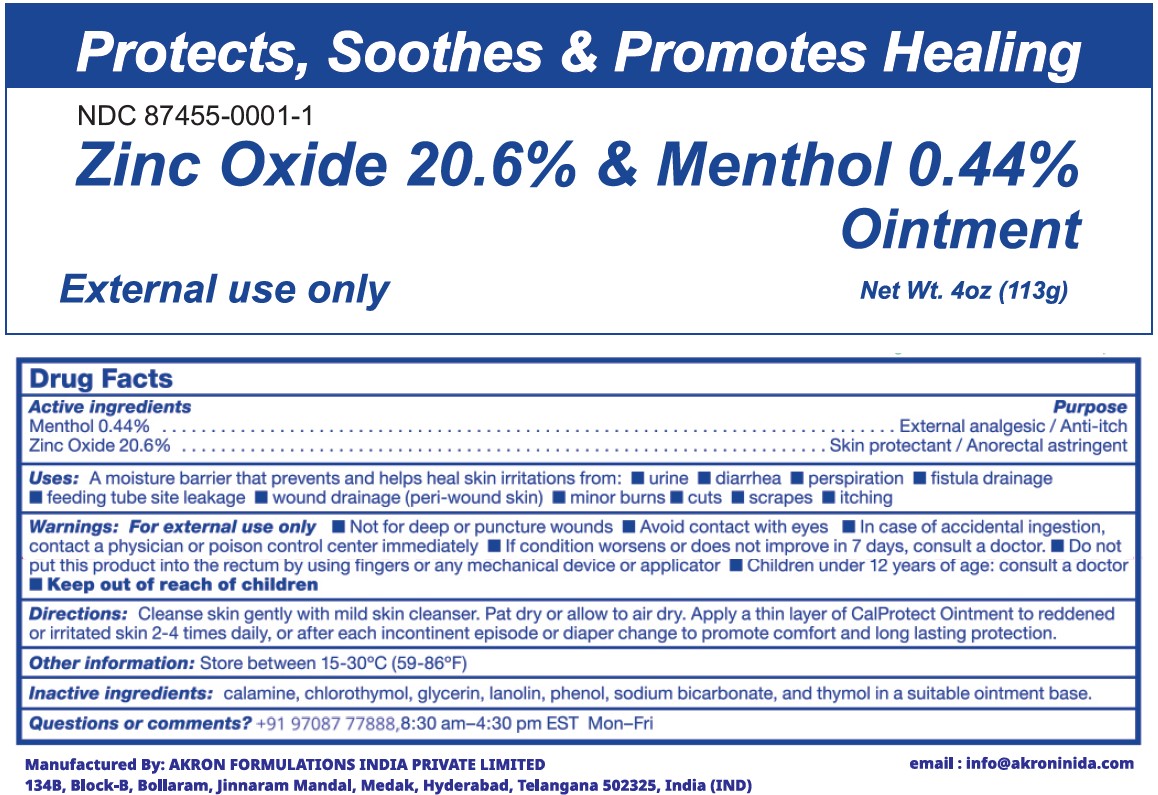 DRUG LABEL: Zinc Oxide and Menthol
NDC: 87455-0001 | Form: OINTMENT
Manufacturer: Akron Formulations India Private Limited
Category: otc | Type: HUMAN OTC DRUG LABEL
Date: 20260223

ACTIVE INGREDIENTS: MENTHOL 0.44 g/100 g; ZINC OXIDE 20.6 g/100 g
INACTIVE INGREDIENTS: FERRIC OXIDE RED; CHLOROTHYMOL; GLYCERIN; LANOLIN; PHENOL; SODIUM BICARBONATE; THYMOL

Zinc Oxide 20.6% & Menthol 0.44% Ointment
Protects, Soothes, Helps Promote Healing

Active Ingredients

Menthol 0.44%

Zinc Oxide 20.6%

Purpose

Active Ingredients Purpose
Menthol 0.44%...........................External analgesic/anti-itch
Zinc Oxide 20.6%......Skin protectant/anorectal astringent

Uses

- A moisture barrier that prevents and heals skin irritations from
- urine
- diarrhea
- prespiration
- fistula drainage
- feeding tube site leakage
- wound drainage (peri-wound skin)
- minor burns
- cuts
- scrapes
- itching

Warnings

For external use only

When using this product

- not for deep or punctured wounds
- avoid contact with eyes

Stop use and ask doctor if

- In case of accidental ingestion contact a physician or Poison Control Center right away
- if condition worsens or does not improve within 7 days, consult a doctor

Directions

Cleanse skin gently with mid skin cleanser. Pat dry or allow to air dry. apply a thin layer of Hydroseptine Ointment to reddened or irritated skin 2-4 times daily, or after each incontinent episode or diaper change to promote comfort and long lasting protection.

Inactive Ingredients:

Other informationstore at room temperature 15-30 C (59-86 F)

Inactive ingredientscalamine, chlorothymol, glycerin, lanoline,phenol, sodium bicarbonate, and thymol,white petrolatum

Questions or Comments?Call toll-free +91 9708777888

Manufactured By:

Akron Formulations India Private Limited

134B, Block-B, Bollaram, Jinnaram Mandal, Medak,

Hyderabad, Telangana 502325, India (IND)

This product is not manufactured or distributed by Calmoseptine Inc., owner of the registered trademark Calmoseptine.